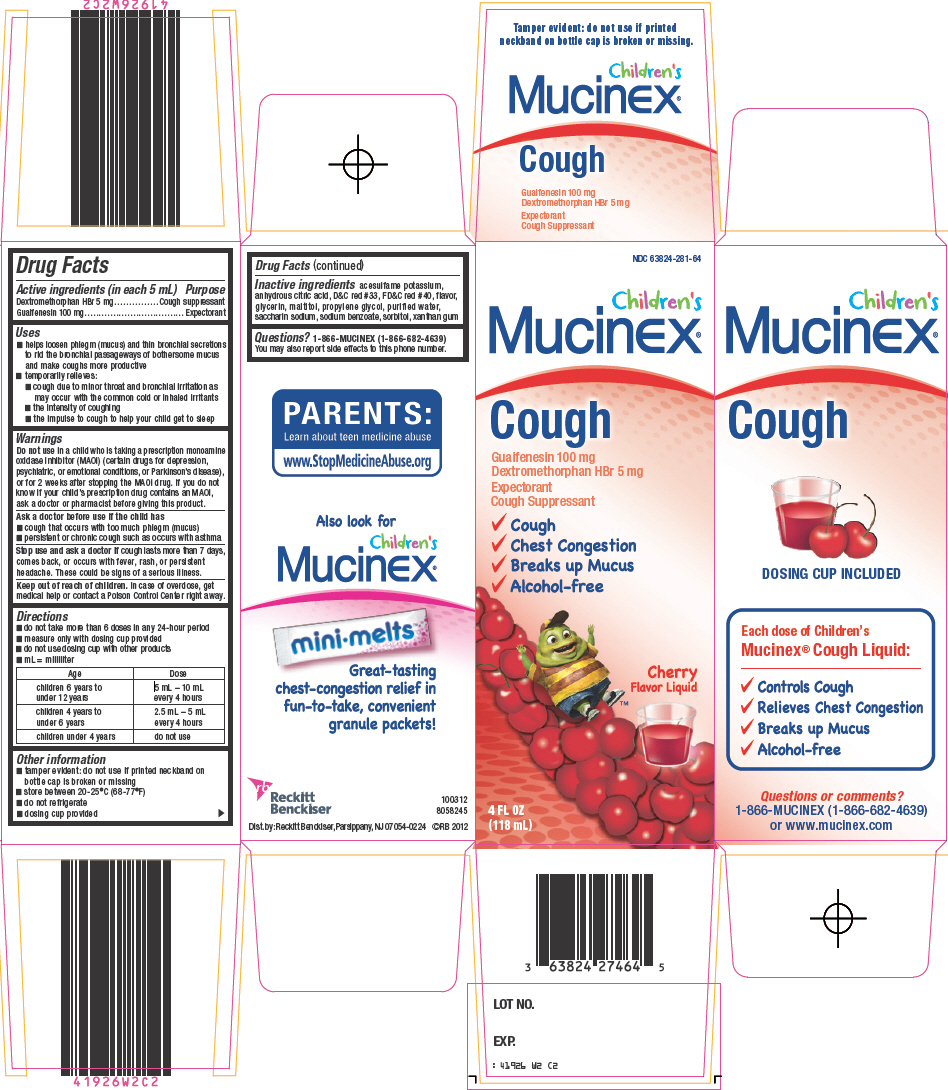 DRUG LABEL: Childrens Mucinex Cough
NDC: 63824-281 | Form: LIQUID
Manufacturer: Reckitt Benckiser LLC
Category: otc | Type: HUMAN OTC DRUG LABEL
Date: 20121109

ACTIVE INGREDIENTS: GUAIFENESIN 100 mg/5 mL; DEXTROMETHORPHAN HYDROBROMIDE 5 mg/5 mL
INACTIVE INGREDIENTS: ACESULFAME POTASSIUM; ANHYDROUS CITRIC ACID; D&C RED NO. 33; FD&C RED NO. 40; GLYCERIN; MALTITOL; PROPYLENE GLYCOL; WATER; SACCHARIN SODIUM; SODIUM BENZOATE; SORBITOL; XANTHAN GUM

Children's
Mucinex®
Cough

Drug Facts

ACTIVE INGREDIENT

Active ingredients (in each 5 mL) | Purpose
Dextromethorphan HBr 5 mg | Cough suppressant
Guaifenesin 100 mg | Expectorant

Uses

- helps loosen phlegm (mucus) and thin bronchial secretions to rid the bronchial passageways of bothersome mucus and make coughs more productive
- temporarily relieves:
  - cough due to minor throat and bronchial irritation as may occur with the common cold or inhaled irritants
  - the intensity of coughing
  - the impulse to cough to help your child get to sleep

Warnings

Do not use in a child who is taking a prescription monoamine oxidase inhibitor (MAOI) (certain drugs for depression, psychiatric, or emotional conditions, or Parkinson's disease), or for 2 weeks after stopping the MAOI drug. If you do not know if your child's prescription drug contains an MAOI, ask a doctor or pharmacist before giving this product.

Ask a doctor before use if the child has

- cough that occurs with too much phlegm (mucus)
- persistent or chronic cough such as occurs with asthma

Stop use and ask a doctor if cough lasts more than 7 days, comes back, or occurs with fever, rash, or persistent headache. These could be signs of a serious illness.

Keep out of reach of children. In case of overdose, get medical help or contact a Poison Control Center right away.

Directions

- do not take more than 6 doses in any 24-hour period
- measure only with dosing cup provided
- do not use dosing cup with other products
- mL = milliliter

Age | Dose
children 6 years to under 12 years | 5 mL – 10 mL every 4 hours
children 4 years to under 6 years | 2.5 mL – 5 mL every 4 hours
children under 4 years | do not use

Other information

- tamper evident: do not use if printed neckband on bottle cap is broken or missing
- store between 20-25°C (68-77°F)
- do not refrigerate
- dosing cup provided

Inactive ingredients

acesulfame potassium, anhydrous citric acid, D&C red #33, FD&C red #40, flavor, glycerin, maltitol, propylene glycol, purified water, saccharin sodium, sodium benzoate, sorbitol, xanthan gum

Questions?

1-866-MUCINEX (1-866-682-4639)

You may also report side effects to this phone number.

Dist. by: Reckitt Benckiser, Parsippany, NJ 07054-0224

PRINCIPAL DISPLAY PANEL - 118 mL Bottle Carton

NDC 63824-281-64

Children's
Mucinex®

Cough

Guaifenesin 100 mg
Dextromethorphan HBr 5 mg

Expectorant
Cough Suppressant

✓Cough
✓Chest Congestion
✓Breaks up Mucus
✓Alcohol-free

Cherry
Flavor Liquid

4 FL OZ
(118 mL)